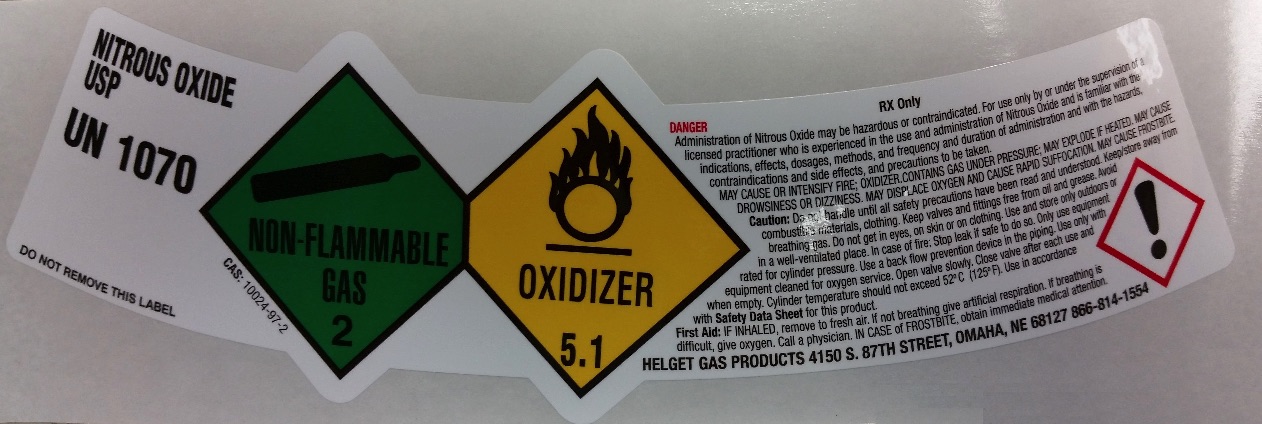 DRUG LABEL: Nitrous Oxide
NDC: 52086-015 | Form: GAS
Manufacturer: Helget Gas Products
Category: prescription | Type: HUMAN PRESCRIPTION DRUG LABEL
Date: 20251112

ACTIVE INGREDIENTS: NITROUS OXIDE 995 mL/1 L

Nitrous Oxide

PACKAGE LABEL

NITROUS OXIDE USP
UN1070
CAS: 10024-97-2
DO NOT REMOVE THIS LABEL
DANGER
RX Only
Administration of Nitrous Oxide may be hazardous or contraindicated. For use only by or under the supervision of a licensed practitioner who is experienced in the use and administration of Nitrous Oxide and is familiar with the indications, effects, dosages, methods, and frequency and duration of administration and with the hazards, contraindications and side effects, and precautions to be taken.
MAY CAUSE OR INTENSIFY FIRE; OXIDIZER. CONTAINS GAS UNDER PRESSURE; MAY EXPLODE IF HEATED. MAY CAUSE DROWSINESS OR DIZZINESS. MAY DISPLACE OXYGEN AND CAUSE RAPID SUFFOCATION. MAY CAUSE FROSTBITE.
Caution: Do not handle until all safety precautions have been read and understood. Keep/store away from combustible materials, clothing. Keep valves and fittings free from oil and grease. Avoid breathing gas. Do not get in eyes, on skin or on clothing. Use and store only outdoors or in a well-ventilated place. In case of fire: Stop leak if safe to do so. Only use equipment rated for cylinder pressure. Use a back flow prevention device in the piping. Use only with equipment cleaned for oxygen service. Open valve slowly. Close valve after each use and when empty. Cylinder temperature should not exceed 52 C (125 F). Use in accordance with Safety Data Sheet for this product.
First Air: IF INHALED, remove to fresh air. If not breathing give artificial respiration. If breathing is difficult, give oxygen. Call a physician. IN CASE of FROSTBITE, obtain immediate medical attention.
HELGET GAS PRODUCTS 4150 S 87TH STREET, OMAHA, NE 68127 866-814-1554